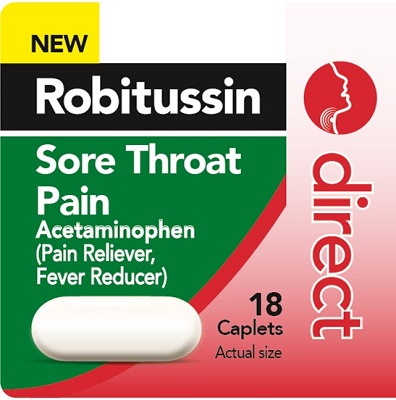 DRUG LABEL: Robitussin Direct Sore Throat Pain
NDC: 0031-9301 | Form: TABLET, COATED
Manufacturer: Haleon US Holdings LLC
Category: otc | Type: HUMAN OTC DRUG LABEL
Date: 20240408

ACTIVE INGREDIENTS: ACETAMINOPHEN 500 mg/1 1
INACTIVE INGREDIENTS: CASTOR OIL; HYPROMELLOSE, UNSPECIFIED; POVIDONE, UNSPECIFIED; STARCH, CORN; SODIUM STARCH GLYCOLATE TYPE A POTATO; STEARIC ACID

Drug Facts

Active ingredient (in each caplet)

Acetaminophen 500 mg

Purposes

Pain reliever/Fever reducer

Uses

- temporarily relieves minor aches and pains due to:
- sore throat
- headache
- backache
- toothache
- premenstrual and menstrual cramps
- the common cold
- minor pain of arthritis
- muscular aches
- temporarily reduces fever

Warnings

Liver warning:

This product contains acetaminophen. Severe liver damage may occur if you take

- more than 4,000 mg of acetaminophen in 24 hours
- with other drugs containing acetaminophen
- 3 or more alcoholic drinks every day while using this product

Allergy alert: Acetaminophen may cause severe skin reactions. Symptoms may include:

- skin reddening
- blisters
- rash
- If a skin reaction occurs, stop use and seek medical help right away.

Do not use

- with any other drug containing acetaminophen (prescription or nonprescription). If you are not sure whether a drug contains acetaminophen, ask a doctor or pharmacist.
- if you are allergic to acetaminophen or any of the inactive ingredients in this product

Stop use and ask a doctor if

- pain gets worse or lasts more than 10 days
- fever gets worse or lasts more than 3 days
- redness or swelling is present
- new symptoms occur
- These could be signs of a serious condition.

Directions

- do not take more than directed
- adults and children 12 years of age and over: take 1 caplet every 4 hours, or 2 caplets every 6 hours, while symptoms last
- do not take more than 6 caplets in any 24 hours, unless directed by a doctor
- do not take for more than 10 days unless directed by a doctor
- children under 12 years of age: ask a doctor

Other information

- store at 25°C (77°F)

Inactive ingredients

castor oil, hypromellose, povidone, pregelatinized starch, sodium starch glycolate, stearic acid

Additional Information

Do not use if safety seal under cap printed with “Sealed for Your Protection” is broken or missing.

Distributed by: GSK Consumer Healthcare, Warren, NJ 07059

visit www.robitussin.com

Trademarks owned or licensed by GSK ©2022 GSK or licensor

Made in China

Lift Here for More Drug Facts

PRINCIPAL DISPLAY PANEL

NEW

Robitussin

Sore Throat Pain

Acetaminophen
(Pain Reliever, Fever Reducer)

direct

18 Caplets

Actual size

L-0630-175-44-UPC_ORG - Front Label